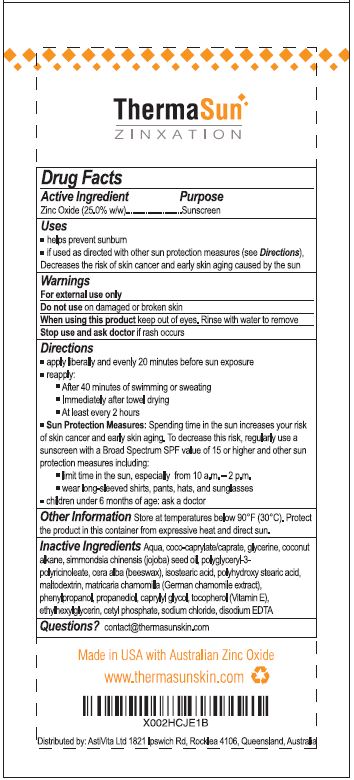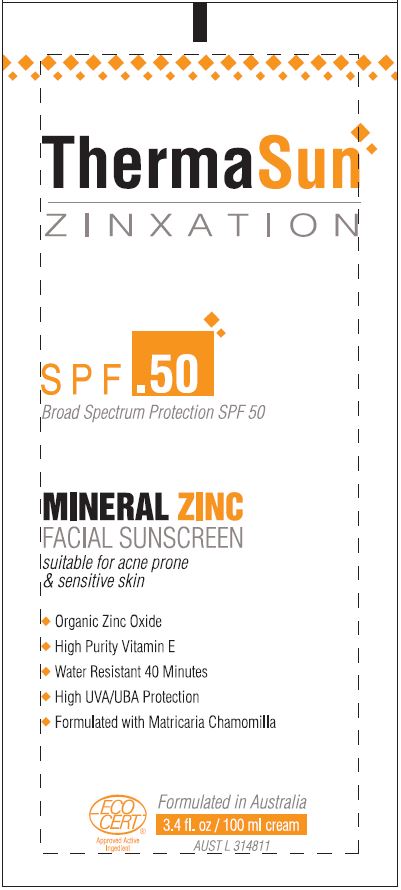 DRUG LABEL: THERMASUN ZINXATION MINERAL ZINC FACIAL SUNSCREEN - ACNE PRONE SKIN
NDC: 80982-002 | Form: LOTION
Manufacturer: ASTIVITA LIMITED
Category: otc | Type: HUMAN OTC DRUG LABEL
Date: 20220127

ACTIVE INGREDIENTS: ZINC OXIDE 25 g/120 g
INACTIVE INGREDIENTS: WATER; COCO-CAPRYLATE/CAPRATE; GLYCERIN; COCONUT ALKANES; JOJOBA OIL; POLYGLYCERYL-3 RICINOLEATE; YELLOW WAX; ISOSTEARIC ACID; POLYHYDROXYSTEARIC ACID (2300 MW); MALTODEXTRIN; MATRICARIA CHAMOMILLA; PHENYLPROPANOL; PROPANEDIOL; CAPRYLYL GLYCOL; TOCOPHEROL; ETHYLHEXYLGLYCERIN; CETYL PHOSPHATE; SODIUM CHLORIDE; EDETATE DISODIUM

THERMASUN ZINXATION MINERAL ZINC FACIAL SUNSCREEN - ACNE-PRONE SKIN - SPF-50

ACTIVE INGREDIENT

ZINC OXIDE (25.0% W/W)

PURPOSE

SUNSCREEN

USES

- Helps prevent sunburn
- If used as directed with other sun protection measures (see Directions), decreased the risk of skin cancer and early skin aging caused by the sun

WARNINGS

For external use only
Do not use on damaged or broken skin
When using this product keep out of eyes. Rinse with water to remove
Stop use and ask doctor if rash occurs

DIRECTIONS

• apply liberally and evenly 20 minutes before sun exposure
• reapply: After 40 minutes of swimming or sweating Immediately after towel drying

- at least every 2 hours

Sun Protection Measures: Spending time in the sun increases your risk of skin cancer and early skin aging. To decrease this risk, regularly use a sunscreen with a Broad Spectrum SPF value of 15 or higher and other sun protection measures including:
• limit time in the sun, especially from 10 a.m. – 2 p.m.
• wear long-sleeved shirts, pants, hats, and sunglasses
• children under 6 months of age: ask a doctor

INACTIVE INGREDIENTS

Aqua, coco-caprylate/caprate, glycerine, coconut alkane, simmondsia chinensis (jojoba) seed oil, polyglyceryl-3-polyricinoleate, cera alba (beeswax), isostearic acid, polyhydroxystearic acid, maltodextrin, matricaria chamomilla (German chamomile extract), phenylpropanol, propanediol, caprylyl glycol, tocopherol (vitamin e), ethylhexylglycerin, cetyl phospate, sodium chloride, disodium EDTA

QUESTIONS?

contact@thermasunskin.com